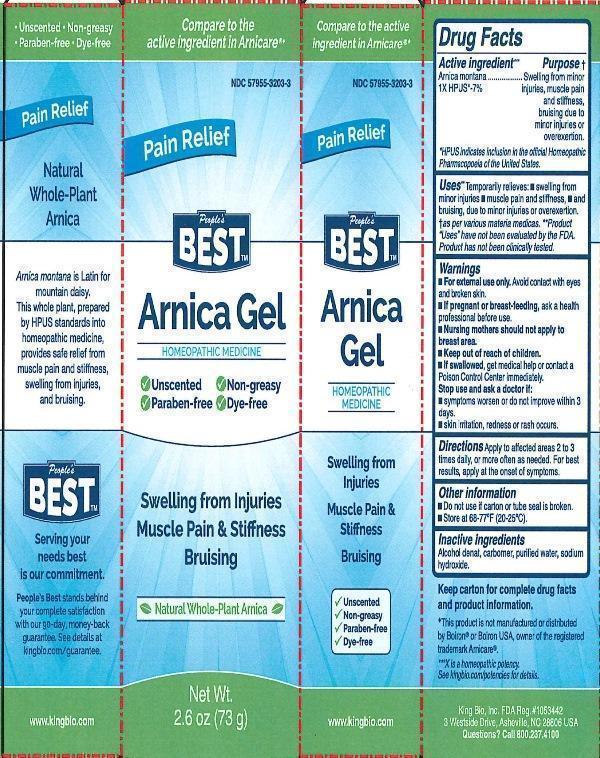 DRUG LABEL: Arnica Gel
NDC: 57955-3203 | Form: GEL
Manufacturer: King Bio Inc.
Category: homeopathic | Type: HUMAN OTC DRUG LABEL
Date: 20160317

ACTIVE INGREDIENTS: ARNICA MONTANA 1 [hp_X]/73 g
INACTIVE INGREDIENTS: ALCOHOL; CARBOMER INTERPOLYMER TYPE A (ALLYL SUCROSE CROSSLINKED); WATER; SODIUM HYDROXIDE

Arnica Gel

ACTIVE INGREDIENT

Drug Facts__________________________________________________________________________________________________________

Active ingredient:

Arnica montana 1X HPUS*-7%

*HPUS indicates inclusion in the official Homeopathic Pharmacopoeia of the United States.

INDICATIONS AND USAGE

Uses Temporarily relieves: •swelling form minor injuries •muscle pain and stiffness, •and bruising, due to minor injuries or overexertion. †as per various materia medicas. Product "Uses" have not been evaluated by the FDA. Product has not been clinically tested.

Warnings:

- For external use only. Avoid contact with eyes and broken skin.
- If pregnant or breast-feeding, ask a health professional before use.
- Nursing mothers should not apply to breast area.
- Keep out of reach of children.
- If swallowed, get medical help or contact a Poison Control Center immediately.
- Stop use and ask a doctor if: •symptoms worsen or do not improve within 3 days •skin irritation, redness or rash occurs.

- Keep out of reach of children.

DOSAGE AND ADMINISTRATION

Directions: Apply to affected areas 2 or 3 times daily, or more often as needed. For best results, apply at the onset of symptoms.

Other information:

- Do not use if carton or tube seal is broken.
- Store at 68-77°F (20-25°C).
- Keep carton for complete drug facts and product information.

INACTIVE INGREDIENT

Inactive ingredients: Alcohol denat, carbomer, purified water, sodium hydroxide.

Drug Facts

____________________________________________________________________________________________________________________

Active ingredients Purpose†

Arnica montana.......................................Swelling from minor injuries, muscle pain and stiffness, bruising due to minor injuries or overexertion.

*HPUS indicates inclusion in the official Homeopathic Pharmacopoeia of the United States.